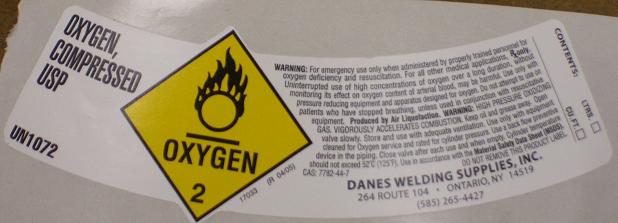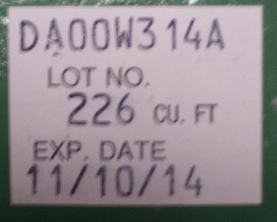 DRUG LABEL: Oxygen
NDC: 65402-0001 | Form: GAS
Manufacturer: Danes Welding Supplies Inc. 
Category: prescription | Type: HUMAN PRESCRIPTION DRUG LABEL
Date: 20091112

ACTIVE INGREDIENTS: Oxygen 99 L/100 L

Oxygen